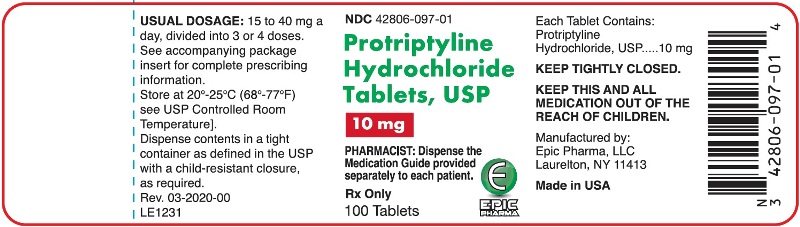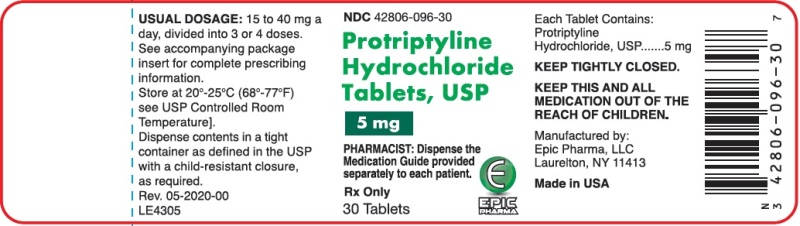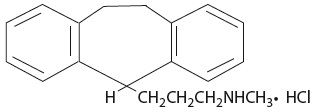 DRUG LABEL: Protriptyline Hydrochloride
NDC: 42806-096 | Form: TABLET, FILM COATED
Manufacturer: Epic Pharma, LLC
Category: prescription | Type: HUMAN PRESCRIPTION DRUG LABEL
Date: 20230725

ACTIVE INGREDIENTS: PROTRIPTYLINE HYDROCHLORIDE 5 mg/1 1
INACTIVE INGREDIENTS: CELLULOSE, MICROCRYSTALLINE; STARCH, TAPIOCA; LACTOSE MONOHYDRATE; CALCIUM PHOSPHATE, DIBASIC, ANHYDROUS; SODIUM STARCH GLYCOLATE TYPE A POTATO; MAGNESIUM STEARATE; HYPROMELLOSES; TRIACETIN; POLYSORBATE 20; TITANIUM DIOXIDE; FD&C YELLOW NO. 6

Protriptyline Hydrochloride Tablets, USP
Rx Only

Boxed Warning

Suicidality and Antidepressant Drugs

Antidepressants increased the risk compared to placebo of suicidal thinking and behavior (suicidality) in children, adolescents, and young adults in short-term studies of major depressive disorder (MDD) and other psychiatric disorders. Anyone considering the use of protriptyline hydrochloride or any other antidepressant in a child, adolescent, or young adult must balance this risk with the clinical need. Short-term studies did not show an increase in the risk of suicidality with antidepressants compared to placebo in adults beyond age 24; there was a reduction in risk with antidepressants compared to placebo in adults aged 65 and older. Depression and certain other psychiatric disorders are themselves associated with increases in the risk of suicide. Patients of all ages who are started on antidepressant therapy should be monitored appropriately and observed closely for clinical worsening, suicidality, or unusual changes in behavior. Families and caregivers should be advised of the need for close observation and communication with the prescriber. Protriptyline hydrochloride is not approved for use in pediatric patients. (See WARNINGS: Clinical Worsening and Suicide Risk, PRECAUTIONS: Information for Patients, and PRECAUTIONS: Pediatric Use.)

DESCRIPTION

Protriptyline HCl is N-methyl-5H dibenzo[a,d]-cycloheptene-5-propanamine hydrochloride. Its molecular formula is C19H21N•HCl and its structural formula is:

Protriptyline HCl, a dibenzocycloheptene derivative, has a molecular weight of 299.84. It is a white to yellowish powder that is freely soluble in water and soluble in dilute HCl. Protriptyline HCl is supplied as 5 mg or 10 mg film-coated tablets. Inactive ingredients are microcrystalline cellulose, pregelatinized starch, lactose monohydrate, dibasic calcium phosphate, sodium starch glycolate, magnesium stearate, hypromellose, triacetin, polysorbate, titanium dioxide and FD & C yellow 6 aluminum lake. The 10 mg tablet also contains polyethylene glycol and polysorbate 80.

CLINICAL PHARMACOLOGY

Protriptyline hydrochloride is an antidepressant agent. The mechanism of its antidepressant action in man is not known. It is not a monoamine oxidase inhibitor, and it does not act primarily by stimulation of the central nervous system.

Protriptyline has been found in some studies to have a more rapid onset of action than imipramine or amitriptyline. The initial clinical effect may occur within one week. Sedative and tranquilizing properties are lacking. The rate of excretion is slow.

INDICATIONS AND USAGE

Protriptyline hydrochloride tablets are indicated for the treatment of symptoms of mental depression in patients who are under close medical supervision. Its activating properties make it particularly suitable for withdrawn and anergic patients.

CONTRAINDICATIONS

Protriptyline hydrochloride tablets are contraindicated in patients who have shown prior hypersensitivity to it.

It should not be given concomitantly with a monoamine oxidase inhibiting compound. Hyperpyretic crises, severe convulsions, and deaths have occurred in patients receiving tricyclic antidepressant and monoamine oxidase inhibiting drugs simultaneously. When it is desired to substitute protriptyline for a monoamine oxidase inhibitor, a minimum of 14 days should be allowed to elapse after the latter is discontinued. Protriptyline should then be initiated cautiously with gradual increase in dosage until optimum response is achieved.

Protriptyline is contraindicated in patients taking cisapride because of the possibility of adverse cardiac interactions including prolongation of the QT interval, cardiac arrhythmias and conduction system disturbances.

This drug should not be used during the acute recovery phase following myocardial infarction.

WARNINGS

Clinical Worsening and Suicide Risk

Patients with major depressive disorder (MDD), both adult and pediatric, may experience worsening of their depression and/or the emergence of suicidal ideation and behavior (suicidality) or unusual changes in behavior, whether or not they are taking antidepressant medications, and this risk may persist until significant remission occurs. Suicide is a known risk of depression and certain other psychiatric disorders, and these disorders themselves are the strongest predictors of suicide. There has been a long-standing concern, however, that antidepressants may have a role in inducing worsening of depression and the emergence of suicidality in certain patients during the early phases of treatment. Pooled analyses of short-term placebo-controlled trials of antidepressant drugs (SSRIs and others) showed that these drugs increase the risk of suicidal thinking and behavior (suicidality) in children, adolescents and young adults (aged 18-24) with major depressive disorder (MDD) and other psychiatric disorders. Short-term studies did not show an increase in the risk of suicidality with antidepressants compared to placebo in adults beyond age 24; there was a reduction with antidepressants compared to placebo in adults aged 65 and older.

The pooled analysis of placebo-controlled trials in children and adolescents with MDD, obsessive compulsive disorder (OCD), or other psychiatric disorders including a total of 24 short-term trials of 9 antidepressant drugs in over 4400 patients. The pooled analyses of placebo-controlled trials in adults with MDD or other psychiatric disorders included a total of 295 short-term trials (median duration of 2 months) of 11 antidepressant drugs in over 77,000 patients. There was considerable variation in risk of suicidality among drugs, but a tendency toward an increase in the younger patients for almost all drugs studied. There were differences in absolute risk of suicidality across the different indications, with the highest incidence in MDD. The risk differences (drug vs placebo), however, were relatively stable within age strata and across indications. These risk differences (drug-placebo difference in the number of cases of suicidality per 1000 patients treated) are provided in Table 1.

Table 1
Age Range | Drug-Placebo Difference in Number of Cases of Suicidality per 1000 Patients Treated; Drug-Related Increases
<18 | 14 additional cases
18-24 | 5 additional cases
 | Drug-Related Decreases
25-64 | 1 fewer case
≥ 65 | 6 fewer cases
Suicidality Cases in Drug-Placebo Patients Per Age Group

No suicides occurred in any of the pediatric trials. There were suicides in the adult trials, but the number was not sufficient to reach any conclusion about drug effect on suicide.

It is unknown whether the suicidality risk extends to longer-term use, i.e., beyond several months. However, there is substantial evidence from placebo-controlled maintenance trials in adults with depression that the use of antidepressants can delay the recurrence of depression.

All patients being treated with antidepressants for any indication should be monitored appropriately and observed closely for clinical worsening, suicidality, and unusual changes in behavior, especially during the initial few months of a course of drug therapy, or at times of dose changes, either increases or decreases.

The following symptoms, anxiety, agitation, panic attacks, insomnia, irritability, hostility, aggressiveness, impulsivity, akathisia (psychomotor restlessness), hypomania, and mania, have been reported in adult and pediatric patients being treated with antidepressants for major depressive disorder as well as for other indications, both psychiatric and nonpsychiatric. Although a causal link between the emergence of such symptoms and either the worsening of depression and/or the emergence of suicidal impulses has not been established, there is concern that such symptoms may represent precursors to emerging suicidality.

Consideration should be given to changing the therapeutic regimen, including possibly discontinuing the medication, in patients whose depression is persistently worse, or who are experiencing emergent suicidality or symptoms that might be precursors to worsening depression or suicidality, especially if these symptoms are severe, abrupt in onset, or were not part of the patient’s presenting symptoms.

If the decision has been made to discontinue treatment, medication should be tapered, as rapidly as is feasible, but with recognition that abrupt discontinuation can be associated with certain symptoms (see ADVERSE REACTIONS - Withdrawal Symptoms for a description of the risks of discontinuation of protriptyline hydrochloride tablets).

Families and caregivers of patients being treated with antidepressants for major depressive disorder or other indications, both psychiatric and nonpsychiatric, should be alerted about the need to monitor patients for the emergence of agitation, irritability, unusual changes in behavior, and the other symptoms described above, as well as the emergence of suicidality, and to report such symptoms immediately to health care providers. Such monitoring should include daily observation by families and caregivers. Prescriptions for protriptyline hydrochloride tablets should be written for the smallest quantity of tablets consistent with good patient management, in order to reduce the risk of overdose.

Screening Patients for Bipolar Disorder:

A major depressive episode may be the initial presentation of bipolar disorder. It is generally believed (though not established in controlled trials) that treating such an episode with an antidepressant alone may increase the likelihood of precipitation of a mixed/manic episode in patients at risk for bipolar disorder. Whether any of the symptoms described above represent such a conversion is unknown. However, prior to initiating treatment with an antidepressant, patients with depressive symptoms should be adequately screened to determine if they are at risk for bipolar disorder; such screening should include a detailed psychiatric history, including a family history of suicide, bipolar disorder, and depression. It should be noted that protriptyline hydrochloride is not approved for use in treating bipolar depression.

Protriptyline may block the antihypertensive effect of guanethidine or similarly acting compounds.

Protriptyline should be used with caution in patients with a history of seizures, and, because of its autonomic activity, in patients with a tendency to urinary retention, or increased intraocular tension.

Tachycardia and postural hypotension may occur more frequently with protriptyline than with other antidepressant drugs. Protriptyline should be used with caution in elderly patients and patients with cardiovascular disorders; such patients should be observed closely because of the tendency of the drug to produce tachycardia, hypotension, arrhythmias, and prolongation of the conduction time. Myocardial infarction and stroke have occurred with drugs of this class.

On rare occasions, hyperthyroid patients or those receiving thyroid medication may develop arrhythmias when this drug is given.

In patients who may use alcohol excessively, it should be borne in mind that the potentiation may increase the danger inherent in any suicide attempt or overdosage.

Angle-Closure Glaucoma

The pupillary dilation that occurs following use of many antidepressant drugs including protriptyline hydrochloride tablets may trigger an angle closure attack in a patient with anatomically narrow angles who does not have a patent iridectomy.

Usage in Pregnancy

Safe use in pregnancy and lactation has not been established; therefore, use in pregnant women, nursing mothers or women who may become pregnant requires that possible benefits be weighed against possible hazards to mother and child.

In mice, rats, and rabbits, doses about ten times greater than the recommended human doses had no apparent adverse effects on reproduction.

PRECAUTIONS

General

When protriptyline HCl is used to treat the depressive component of schizophrenia, psychotic symptoms may be aggravated. Likewise, in manic-depressive psychosis, depressed patients may experience a shift toward the manic phase if they are treated with an antidepressant drug. Paranoid delusions, with or without associated hostility, may be exaggerated. In any of these circumstances, it may be advisable to reduce the dose of protriptyline or to use a major tranquilizing drug concurrently.

Symptoms, such as anxiety or agitation, may be aggravated in overactive or agitated patients.

The possibility of suicide in depressed patients remains during treatment and until significant remission occurs. This type of patient should not have access to large quantities of the drug.

Concurrent administration of protriptyline and electroshock therapy may increase the hazards of therapy. Such treatment should be limited to patients for whom it is essential.

Discontinue the drug several days before elective surgery, if possible.

Both elevation and lowering of blood sugar levels have been reported.

Information for Patients

Prescribers or other health professionals should inform patients, their families and their caregivers about the benefits and risks associated with treatment with protriptyline hydrochloride and should counsel them in its appropriate use. A patient Medication Guide about “Antidepressant Medicines, Depression and other Serious Mental Illness, and Suicidal Thoughts or Actions” is available for protriptyline hydrochloride. The prescriber or health professional should instruct patients, their families, and their caregivers to read the Medication Guide and should assist them in understanding its contents. Patients should be given the opportunity to discuss the contents of the Medication Guide and to obtain answers to any questions they may have. The complete text of the Medication Guide is reprinted at the end of this document.

Patients should be advised of the following issues and asked to alert their prescriber if these occur while taking protriptyline hydrochloride.

Patients should be advised that taking protriptyline hydrochloride tablets can cause mild pupillary dilation, which in susceptible individuals, can lead to an episode of angle-closure glaucoma. Pre-existing glaucoma is almost always open-angle glaucoma because angle-closure glaucoma, when diagnosed, can be treated definitively with iridectomy. Open angle glaucoma is not a risk factor for angle closure glaucoma. Patients may wish to be examined to determine whether they are susceptible to angle closure, and have a prophylactic procedure (e.g., iridectomy), if they are susceptible.

Clinical Worsening and Suicide Risk

Patients, their families, and their caregivers should be encouraged to be alert to the emergence of anxiety, agitation, panic attacks, insomnia, irritability, hostility, aggressiveness, impulsivity, akathisia (psychomotor restlessness), hypomania, mania, other unusual changes in behavior, worsening of depression, and suicidal ideation, especially early during antidepressant treatment and when the dose is adjusted up or down. Families and caregivers of patients should be advised to look for the emergence of such symptoms on a day-to-day basis, since changes may be abrupt. Such symptoms should be reported to the patient’s prescriber or health professional, especially if they are severe, abrupt in onset, or were not part of the patient’s presenting symptoms. Symptoms such as these may be associated with an increased risk for suicidal thinking and behavior and indicate a need for very close monitoring and possibly changes in the medication.

While on therapy with protriptyline, patients should be advised as to the possible impairment of mental and/or physical abilities required for performance of hazardous tasks, such as operating machinery or driving a motor vehicle.

Drug Interactions

When protriptyline is given with anticholinergic agents or sympathomimetic drugs, including epinephrine combined with local anesthetics, close supervision and careful adjustment of dosages are required.

Hyperpyrexia has been reported when tricyclic antidepressants are administered with anticholinergic agents or with neuroleptic drugs, particularly during hot weather.

Cimetidine is reported to reduce hepatic metabolism of certain tricyclic antidepressants, thereby delaying elimination and increasing steady-state concentrations of these drugs. Clinically significant effects have been reported with the tricyclic antidepressants when used concomitantly with cimetidine. Increases in plasma levels of tricyclic antidepressants, and in the frequency and severity of side-effects, particularly anticholinergic, have been reported when cimetidine was added to the drug regimen. Discontinuation of cimetidine in well-controlled patients receiving tricyclic antidepressants and cimetidine may decrease the plasma levels and efficacy of the antidepressants.

Tricyclic antidepressants may enhance the seizure risk in patients taking ULTRAM (tramadol hydrochloride).

Protriptyline may enhance the response to alcohol and the effects of barbiturates and other CNS depressants.

Drugs Metabolized by Cytochrome P450 2D6

The biochemical activity of the drug metabolizing isozyme cytochrome P450 2D6 (debrisoquine hydroxylase) is reduced in a subset of the Caucasian population (about 7% to 10% of Caucasians are so called “poor metabolizers”); reliable estimates of the prevalence of reduced P450 2D6 isozyme activity among Asian, African, and other populations are not yet available. Poor metabolizers have higher than expected plasma concentrations of tricyclic antidepressants (TCAs) when given usual doses. Depending on the fraction of drug metabolized by P450 2D6, the increase in plasma concentration may be small or quite large (8 fold increase in plasma AUC of the TCA).

In addition, certain drugs inhibit the activity of this isozyme and make normal metabolizers resemble poor metabolizers. An individual who is stable on a given dose of TCA may become abruptly toxic when given one of these inhibiting drugs as concomitant therapy. The drugs that inhibit cytochrome P450 2D6 include some that are not metabolized by the enzyme (quinidine; cimetidine) and many that are substrates for P450 2D6 (many other antidepressants, phenothiazines, and the Type 1C antiarrhythmics, propafenone and flecainide). While all the selective serotonin reuptake inhibitors (SSRIs), e.g., fluoxetine, sertraline, and paroxetine, inhibit P450 2D6, they may vary in the extent of inhibition. The extent to which SSRI-TCA interactions may pose clinical problems will depend on the degree of inhibition and the pharmacokinetics of the SSRI involved. Nevertheless, caution is indicated in the coadministration of TCAs with any of the SSRIs and also in switching from one class to the other. Of particular importance, sufficient time must elapse before initiating TCA treatment in a patient being withdrawn from fluoxetine, given the long half-life of the parent and active metabolite (at least 5 weeks may be necessary).

Concomitant use of tricyclic antidepressants with drugs that can inhibit cytochrome P450 2D6 may require lower doses than usually prescribed for either the tricyclic antidepressant or the other drug. Furthermore, whenever one of these other drugs is withdrawn from co-therapy, an increased dose of tricyclic antidepressant may be required. It is desirable to monitor TCA plasma levels whenever a TCA is going to be coadministered with another drug known to be an inhibitor of P450 2D6.

Pediatric Use

Safety and effectiveness in the pediatric population have not been established (see BOX WARNINGS and WARNINGS – Clinical Worsening and Suicide Risk). Anyone considering the use of protriptyline hydrochloride in a child or adolescent must balance the potential risks with the clinical need.

Geriatric Use

Clinical studies of protriptyline did not include sufficient numbers of subjects aged 65 and over to determine whether they respond differently from younger subjects. Other reported clinical experience has not identified differences in responses between the elderly and younger patients. In general, dose selection for an elderly patient should be cautious, usually starting at the low end of the dosing range, reflecting the greater frequency of decreased hepatic, renal, or cardiac function, and of concomitant disease or other drug therapy. (see WARNINGS, DOSAGE AND ADMINISTRATION, and ADVERSE REACTIONS.)

ADVERSE REACTIONS

To report SUSPECTED ADVERSE REACTIONS, contact Epic Pharma, LLC at 1-888-374-2791, or FDA at 1-800-FDA-1088 or www.fda.gov/medwatch.

Within each category the following adverse reactions are listed in order of decreasing severity. Included in the listing are a few adverse reactions which have not been reported with this specific drug. However, the pharmacological similarities among the tricyclic antidepressant drugs require that each of the reactions be considered when protriptyline is administered. Protriptyline is more likely to aggravate agitation and anxiety and produce cardiovascular reactions such as tachycardia and hypotension.

Cardiovascular:

Myocardial infarction; stroke; heart block; arrhythmias; hypotension, particularly orthostatic hypotension; hypertension; tachycardia; palpitation.

Psychiatric:

Confusional states (especially in the elderly) with hallucinations, disorientation, delusions, anxiety, restlessness, agitation; hypomania; exacerbation of psychosis; insomnia, panic, and nightmares.

Neurological:

Seizures; incoordination; ataxia; tremors; peripheral neuropathy; numbness, tingling, and paresthesias of extremities; extrapyramidal symptoms; drowsiness; dizziness; weakness and fatigue; headache; syndrome of inappropriate ADH (antidiuretic hormone) secretion; tinnitus; alteration in EEG patterns.

Anticholinergic

Paralytic ileus; hyperpyrexia; urinary retention, delayed micturition, dilatation of the urinary tract; constipation; blurred vision, disturbance of accommodation, increased intraocular pressure, mydriasis; dry mouth and rarely associated sublingual adenitis.

Allergic

Drug fever; petechiae, skin rash, urticaria, itching, photosensitization (avoid excessive exposure to sunlight); edema (general, or of face and tongue).

Hematologic:

Agranulocytosis; bone marrow depression; leukopenia; thrombocytopenia; purpura; eosinophilia.

Gastrointestinal:

Nausea and vomiting; anorexia; epigastric distress; diarrhea; peculiar taste; stomatitis; abdominal cramps; black tongue.

Endocrine:

Impotence, increased or decreased libido; gynecomastia in the male; breast enlargement and galactorrhea in the female; testicular swelling; elevation or depression of blood sugar levels.

Other:

Jaundice (simulating obstructive); altered liver function; parotid swelling; alopecia; flushing; weight gain or loss; urinary frequency, nocturia; perspiration.

Withdrawal Symptoms:

Though not indicative of addiction, abrupt cessation of treatment after prolonged therapy may produce nausea, headache, and malaise.

OVERDOSAGE

Deaths may occur from overdosage with this class of drugs. Multiple drug ingestion (including alcohol) is common in deliberate tricyclic antidepressant overdose. As management of overdose is complex and changing, it is recommended that the physician contact a poison control center for current information on treatment. Signs and symptoms of toxicity develop rapidly after tricyclic antidepressant overdose, therefore, hospital monitoring is required as soon as possible.

MANIFESTATIONS

Critical manifestations of overdosage include: cardiac dysrhythmias, severe hypotension, convulsions, and CNS depression, including coma. Changes in the electrocardiogram, particularly in QRS axis or width, are clinically significant indicators of tricyclic antidepressant toxicity.

Other signs of overdose may include: confusion, disturbed concentration, transient visual hallucinations, dilated pupils, agitation, hyperactive reflexes, stupor, drowsiness, muscle rigidity, vomiting, hypothermia, hyperpyrexia, or any of the symptoms listed under ADVERSE REACTIONS.

MANAGEMENT

General

Obtain an ECG and immediately initiate cardiac monitoring. Protect the patient’s airway, establish an intravenous line and initiate gastric decontamination. A minimum of six hours of observation with cardiac monitoring and observation for signs of CNS or respiratory depression, hypotension, cardiac dysrhythmias and/or conduction blocks, and seizures is necessary. If signs of toxicity occur at any time during this period, extended monitoring is required. There are case reports of patients succumbing to fatal dysrhythmias late after overdose. These patients had clinical evidence of significant poisoning prior to death and most received inadequate gastrointestinal decontamination. Monitoring of plasma drug levels should not guide management of the patient.

Gastrointestinal Decontamination

All patients suspected of a tricyclic antidepressant overdose should receive gastro-intestinal decontamination. This should include large volume gastric lavage followed by activated charcoal. If consciousness is impaired, the airway should be secured prior to lavage. Emesis is contraindicated.

Cardiovascular

A maximal limb-lead QRS duration of ≥0.10 seconds may be the best indication of the severity of the overdose. Intravenous sodium bicarbonate should be used to maintain the serum pH in the range of 7.45 to 7.55. If the pH response is inadequate, hyperventilation may also be used. Concomitant use of hyperventilation and sodium bicarbonate should be done with extreme caution, with frequent pH monitoring. A pH >7.60 or a pCO2 <20 mmHg is undesirable. Dysrhythmias unresponsive to sodium bicarbonate therapy/ hyperventilation may respond to lidocaine, bretylium or phenytoin. Type 1A and 1C antiarrhythmics are generally contraindicated (e.g., quinidine, disopyramide, and procainamide).

In rare instances, hemoperfusion may be beneficial in acute refractory cardiovascular instability in patients with acute toxicity. However, hemodialysis, peritoneal dialysis, exchange transfusions, and forced diuresis generally have been reported as ineffective in tricyclic antidepressant poisoning.

CNS

In patients with CNS depression, early intubation is advised because of the potential for abrupt deterioration. Seizures should be controlled with benzodiazepines or, if these are ineffective, other anticonvulsants (e.g., phenobarbital, phenytoin). Physostigmine is not recommended except to treat life-threatening symptoms that have been unresponsive to other therapies, and then only in close consultation with a poison control center.

PSYCHIATRIC FOLLOW-UP:

Since overdosage is often deliberate, patients may attempt suicide by other means during the recovery phase. Psychiatric referral may be appropriate.

PEDIATRIC MANAGEMENT

The principles of management of child and adult overdosages are similar. It is strongly recommended that the physician contact the local poison control center for specific pediatric treatment.

DOSAGE AND ADMINISTRATION

Dosage should be initiated at a low level and increased gradually, noting carefully the clinical response and any evidence of intolerance.

Usual Adult Dosage

Fifteen to 40 mg a day divided into 3 or 4 doses. If necessary, dosage may be increased to 60 mg a day. Dosages above this amount are not recommended. Increases should be made in the morning dose.

Adolescent and Elderly Patients

In general, lower dosages are recommended for these patients. Five mg 3 times a day may be given initially, and increased gradually if necessary. In elderly patients, the cardiovascular system must be monitored closely if the daily dose exceeds 20 mg.

When satisfactory improvement has been reached, dosage should be reduced to the smallest amount that will maintain relief of symptoms.

Minor adverse reactions require reduction in dosage. Major adverse reactions or evidence of hypersensitivity require prompt discontinuation of the drug.

The safety and effectiveness of protriptyline in pediatric patients have not been established.

HOW SUPPLIED

Protriptyline Hydrochloride Tablets USP, 5 mg are dark orange, round biconvex, film coated tablets, de-bossed “Є96” on one side, and plain on the other side, available in bottles of 30 (NDC: 42806-096-30), in bottles of 100 (NDC: 42806-096-01) and in bottles of 1000 (NDC: 42806-096-10).

Protriptyline Hydrochloride Tablets USP, 10 mg are light orange, round biconvex, film coated tablets, de-bossed “Є97” on one side, and plain on the other side, available in bottles of 30 (NDC: 42806-097-30), in bottles of 100 (NDC: 42806-097-01) and in bottles of 1000 (NDC: 42806-097-10).

Dispense in a tight container as defined in the USP.

Store at 20°-25°C (68°-77°F) [See USP Controlled Room Temperature].

METABOLISM

Metabolic studies indicate that protriptyline is well absorbed from the gastrointestinal tract and is rapidly sequestered in tissues. Relatively low plasma levels are found after administration, and only a small amount of unchanged drug is excreted in the urine of dogs and rabbits. Preliminary studies indicate that demethylation of the secondary amine moiety occurs to a significant extent, and that metabolic transformation probably takes place in the liver. It penetrates the brain rapidly in mice and rats, and moreover that which is present in the brain is almost all unchanged drug.

Studies on the disposition of radioactive protriptyline in human test subjects showed significant plasma levels within 2 hours, peaking at 8 to 12 hours, then declining gradually.

Urinary excretion studies in the same subjects showed significant amounts of radioactivity in 2 hours. The rate of excretion was slow. Cumulative urinary excretion during 16 days accounted for approximately 50% of the drug. The fecal route of excretion did not seem to be important.

Dispense with Medication Guide available at:www.epic-pharma.com/medguide/Protriptyline-Hydrochloride-Tablet.pdf

Dispense with Medication Guide available at:www.epic-pharma.com/medguide/Protriptyline-Hydrochloride-Tablet.pdf Medication Guide Protriptyline Hydrochloride Tablets, USP

Antidepressant Medicines, Depression and other Serious Mental Illnesses, and Suicidal Thoughts or Actions

Read the Medication Guide that comes with you or your family member’s antidepressant medicine. This Medication Guide is only about the risk of suicidal thoughts and actions with antidepressant medicines. Talk to your, or your family member’s, healthcare provider about:

- all risks and benefits of treatment with antidepressant medicines
- all treatment choices for depression or other serious mental illness

What is the most important information I should know about antidepressant medicines, depression and other serious mental illnesses, and suicidal thoughts or actions?

1. Antidepressant medicines may increase suicidal thoughts or actions in some children, teenagers, and young adults when the medicine is first started.
2. Depression and other serious mental illnesses are the most important causes of suicidal thoughts and actions. Some people may have a particularly high risk of having suicidal thoughts or actions. These include people who have (or have a family history of) bipolar illness (also called manic-depressive illness) or suicidal thoughts or actions.

How can I watch for and try to prevent suicidal thoughts and actions in myself or a family member?

- Pay close attention to any changes, especially sudden changes, in mood, behaviors, thoughts, or feelings. This is very important when an antidepressant medicine is first started or when the dose is changed.
- Call the healthcare provider right away to report new or sudden changes in mood, behavior, thoughts, or feelings.
- Keep all follow-up visits with the healthcare provider as scheduled. Call the healthcare provider between visits as needed, especially if you have concerns about your symptoms.

Call a healthcare provider right away if you or your family member has any of the following symptoms, especially if they are new, worse, or worry you:

- thoughts about suicide or dying
- attempts to commit suicide
- new or worse depression
- new or worse anxiety
- feeling very agitated or restless
- panic attacks
- trouble sleeping (insomnia)
- new or worse irritability
- acting aggressive, being angry, or violent
- acting on dangerous impulses
- an extreme increase in activity and talking (mania)
- other unusual changes in behavior or mood
- visual problems: eye pain, changes in vision, swelling or redness in or around the eye

What else do I need to know about antidepressant medicines?

- Never stop an antidepressant medicine without first talking to a healthcare

provider. Stopping an antidepressant medicine suddenly can cause other symptoms.

- Visual problems.Only some people are at risk for these problems. You may want to undergo an eye examination to see if you are at risk and receive preventative treatment if you are.
- Antidepressants are medicines used to treat depression and other illnesses. It is important to discuss all the risks of treating depression and also the risks of not treating it. Patients and their families or other caregivers should discuss all treatment choices with the healthcare provider, not just the use of antidepressants.

- Antidepressant medicines have other side effects. Talk to the healthcare provider about the side effects of the medicine prescribed for you or your family member.

- Antidepressant medicines can interact with other medicines. Know all of the medicines that you or your family member takes. Keep a list of all medicines to show the healthcare provider. Do not start new medicines without first checking with your healthcare provider.

- Not all antidepressant medicines prescribed for children are FDA approved for use in children. Talk to your child's healthcare provider for more information.

This Medication Guide has been approved by the U.S. Food and Drug Administration for all antidepressants.

These are not all the possible side effects. Call your doctor for medical advice about side effects. You may report side effects to FDA at 1-800-FDA-1088.

You may also report side effects to Epic Pharma, LLC at 1-888-374-2791.

Manufactured by:

Epic Pharma, LLC

Laurelton, NY 11413

Made in USA

Rev. 07-2023-00

MF096REV07/23

OE1049

PRINCIPAL DISPLAY PANEL

Protriptyline Hydrochloride Tablets, USP

5 mg - 30 Tablets

Rx Only

PRINCIPAL DISPLAY PANEL

Protriptyline Hydrochloride Tablets, USP

10 mg - 100 Tablets

Rx Only